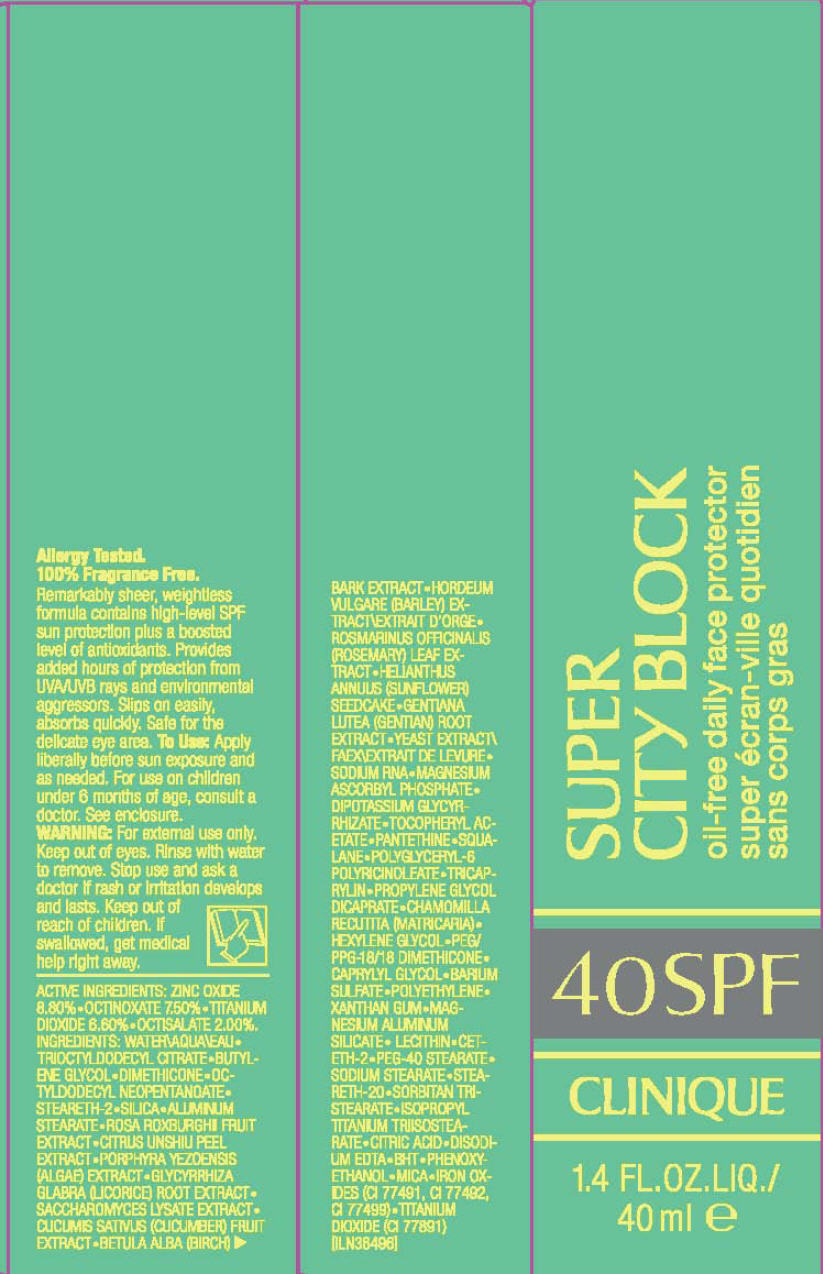 DRUG LABEL: SUPER CITY BLOCK 
NDC: 49527-942 | Form: CREAM
Manufacturer: CLINIQUE  LABORATORIES INC.
Category: otc | Type: HUMAN OTC DRUG LABEL
Date: 20110915

ACTIVE INGREDIENTS: zinc oxide 8.8 mL/100 mL; octinoxate 7.5 mL/100 mL; titanium dioxide 6.6 mL/100 mL; octisalate 2 mL/100 mL
INACTIVE INGREDIENTS: water; butylene glycol; dimethicone; octyldodecyl neopentanoate; steareth-2; silicon dioxide; aluminum stearate; angelica acutiloba root; jujube fruit; rosa roxburghii fruit; tangerine peel; porphyra yezoensis; paeonia suffruticosa root; safflower; glycyrrhiza glabra; paeonia lactiflora root; saccharomyces lysate; cucumber; betula pubescens bark; hordeum vulgare root; rosemary; helianthus annuus seedcake; gentiana lutea root; yeast; magnesium ascorbyl phosphate; glycyrrhizinate dipotassium; pantethine; glycerin; dextrose; squalane; tricaprylin; propylene glycol dicaprate; hexylene glycol; caprylyl glycol; barium sulfate; high density polyethylene; xanthan gum; magnesium aluminum silicate; ceteth-2; peg-40 stearate; sodium stearate; steareth-20; sorbitan tristearate; citric acid monohydrate; edetate disodium; butylated hydroxytoluene; phenoxyethanol; mica; ferric oxide red; ferric oxide yellow; ferrosoferric oxide; fu ling; ALPHA-TOCOPHEROL ACETATE; CHAMOMILE; LECITHIN, SOYBEAN

SUPER
CITY BLOCK
oil-free daily face protector

To Use

Apply liberally before sun exposure and as needed. For use on children under 6 months of age, consult a doctor. See enclosure.

WARNING

For external use only.

WHEN USING

Keep out of eyes. Rinse with water to remove.

Stop use and ask a doctor if rash or irritation develops and lasts.

Keep out of reach of children. If swallowed, get medical help right away.

ACTIVE INGREDIENTS

ZINC OXIDE 8.80% • OCTINOXATE 7.5% • TITANIUM DIOXIDE 6.60% • OCTISALATE 2.00%.

INGREDIENTS

WATER\AQUA\EAU • TRIOCTYLDODECYL CITRATE • BUTYLENE GLYCOL • DIMETHICONE • OCTYLDODECYL NEOPENTANOATE • STEARETH-2 • SILICA • ALUMINUM STEARATE • ROSA ROXBURGHII FRUIT EXTRACT • CITRUS UNSHIU PEEL EXTRACT • PORPHYRA YEZOENSIS (ALGAE) EXTRACT • GLYCYRRHIZA GLABRA (LICORICE) ROOT EXTRACT • SACCHAROMYCES LYSATE EXTRACT • CUCUMIS SATIVUS (CUCUMBER) FRUIT EXTRACT • BETULA ALBA (BIRCH) BARK EXTRACT • HORDEUM VULGARE (BARLEY) EXTRACT\EXTRAIT D'ORGE • ROSMARINUS OFFICINALIS (ROSEMARY) LEAF EXTRACT • HELIANTHUS ANNULIS (SUNFLOWER) SEEDCAKE • GENTIANA LUTEA (GENTIAN) ROOT EXTRACT • YEAST EXTRACT\FAEX\EXTRAIT DE LEVURE • SODIUM RNA • MAGNESIUM ASCORBYL PHOSPHATE • DIPOTASSIUM GLYCYRRHIZATE • TOCOPHERYL ACETATE • PANTETHINE • SQUALANE • POLYGLYCERYL-6 POLYRICINOLEATE • TRICAPRYLIN • PROPYLENE GLYCOL DICAPRATE • CHAMOMILLA RECUTTIA (MATRICARIA) • HEXYLENE GLYCOL • PEG/PPG-18/18 DIMETHICONE • CAPRYLYL GLYCOL • BARIUM SULFATE • POLYETHYLENE • XANTHAN GUM • MAGNESIUM ALUMINUM SILICATE • LECITHIN • CETETH-2 • PEG-40 STEARATE • SODIUM STEARATE • STEARETH-20 • SORBITAN TRISTEARATE • ISOPROPYL TITANIUM TRIISOSTEARATE • CITRIC ACID • DISODIUM EDTA • BHT • PHENOXYETHANOL • MICA • IRON OXIDES (CI 77491, CI 77492, CI77499) • TITANIUM DIOXIDE (CI 77891) [ILN38498]

PRINCIPAL DISPLAY PANEL - 40 ml Carton

SUPER
CITY BLOCK
oil-free daily face protector

40SPF

CLINIQUE

1.4 FL.OZ.LIQ./
40 ml e